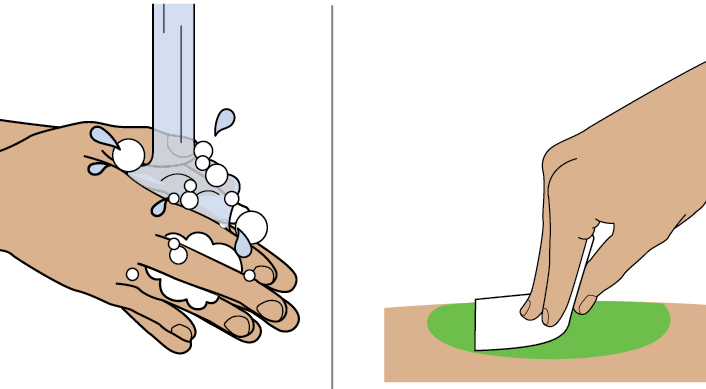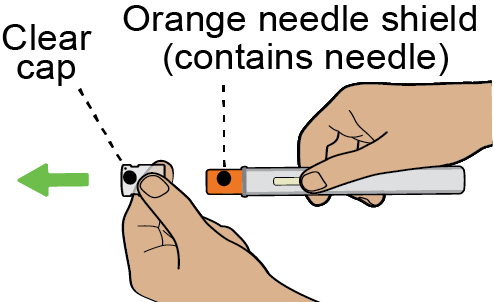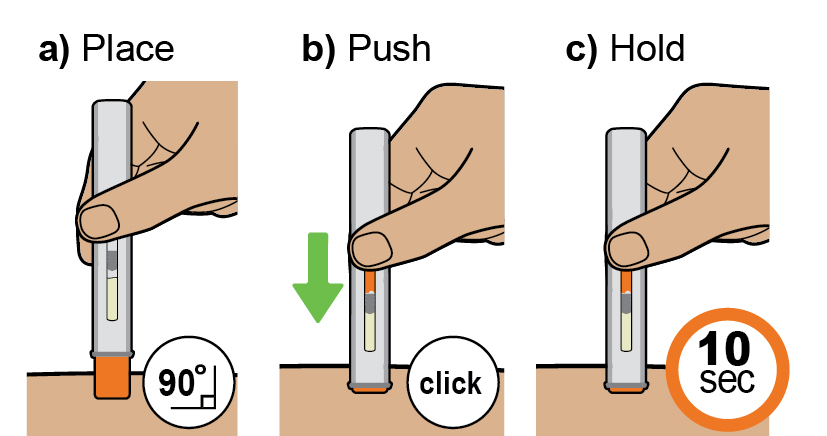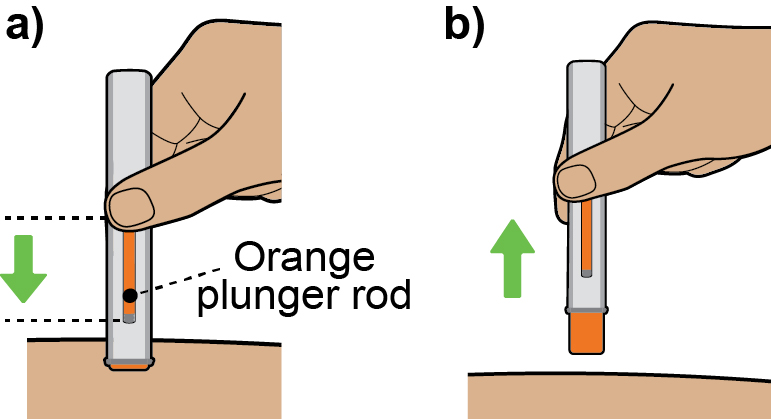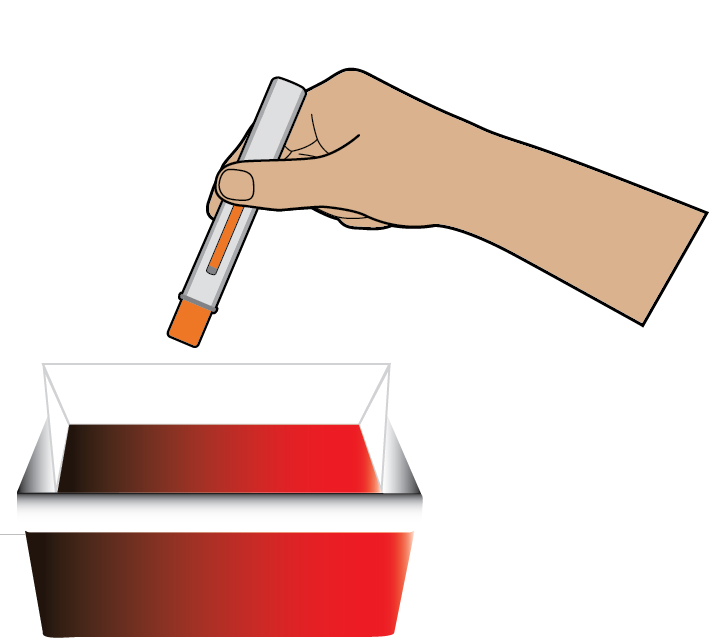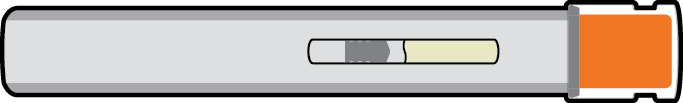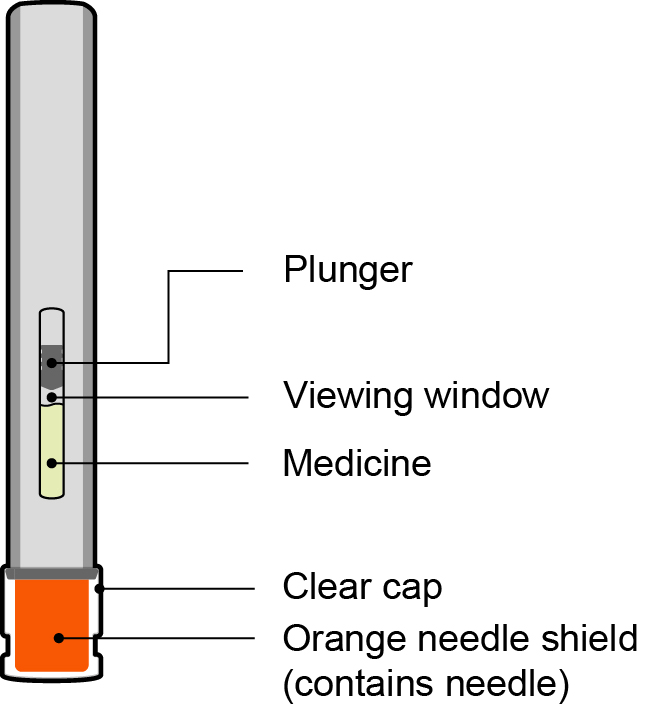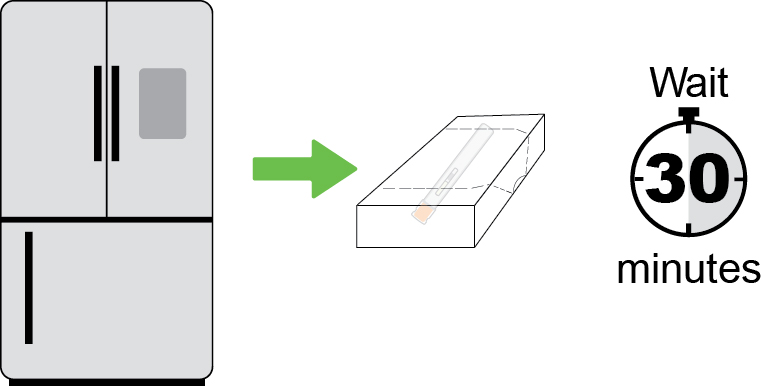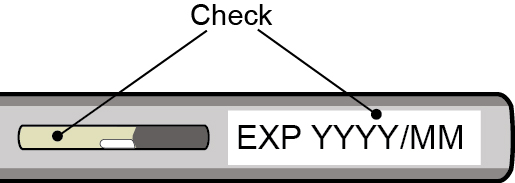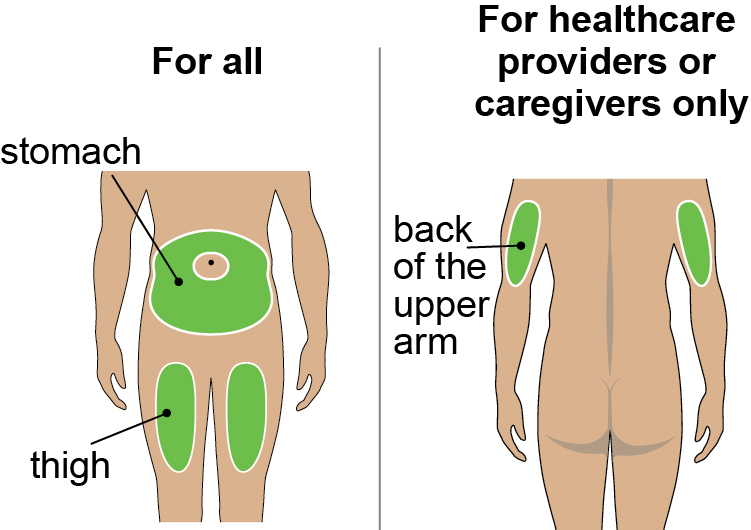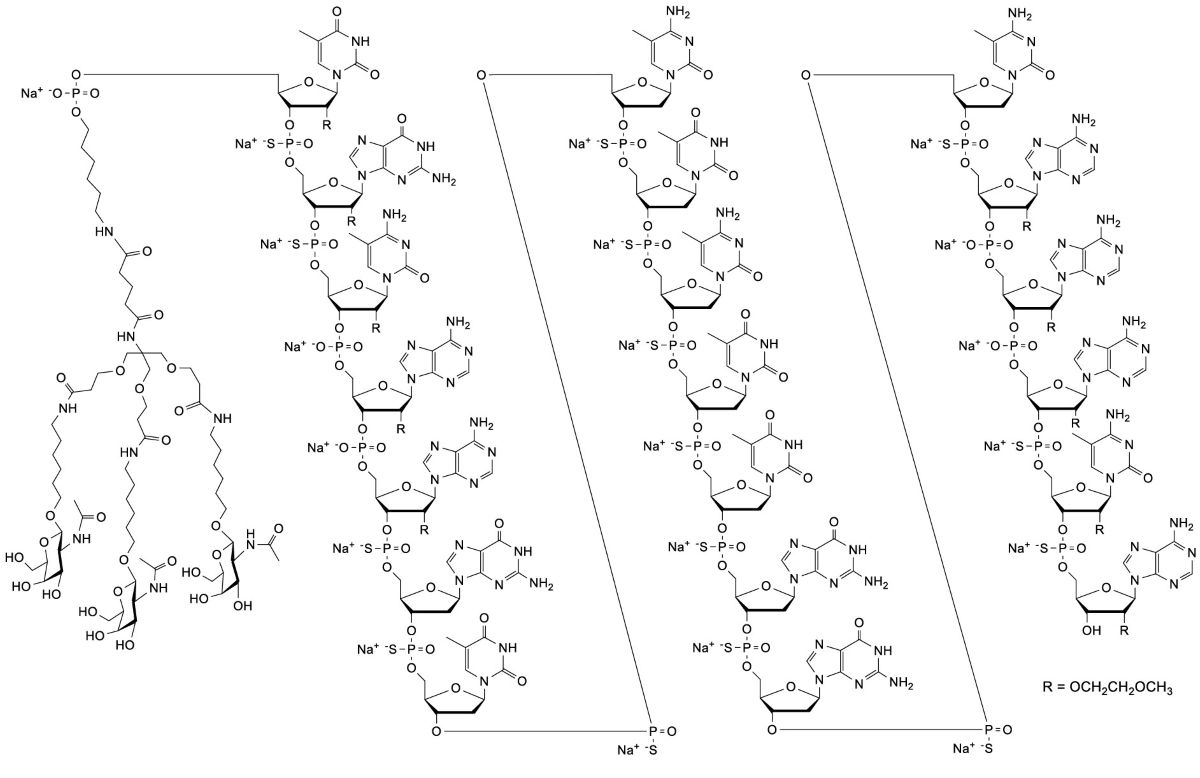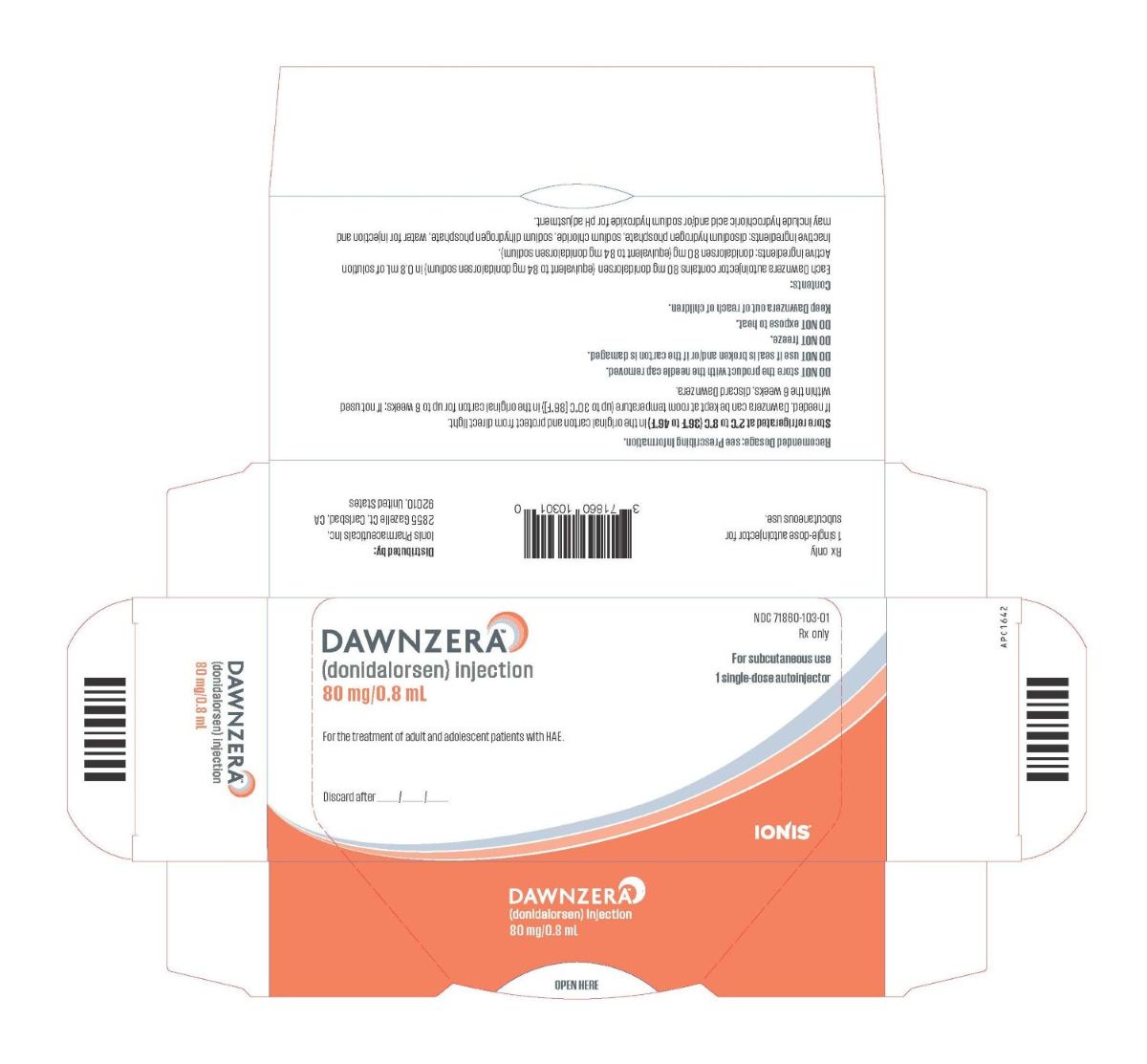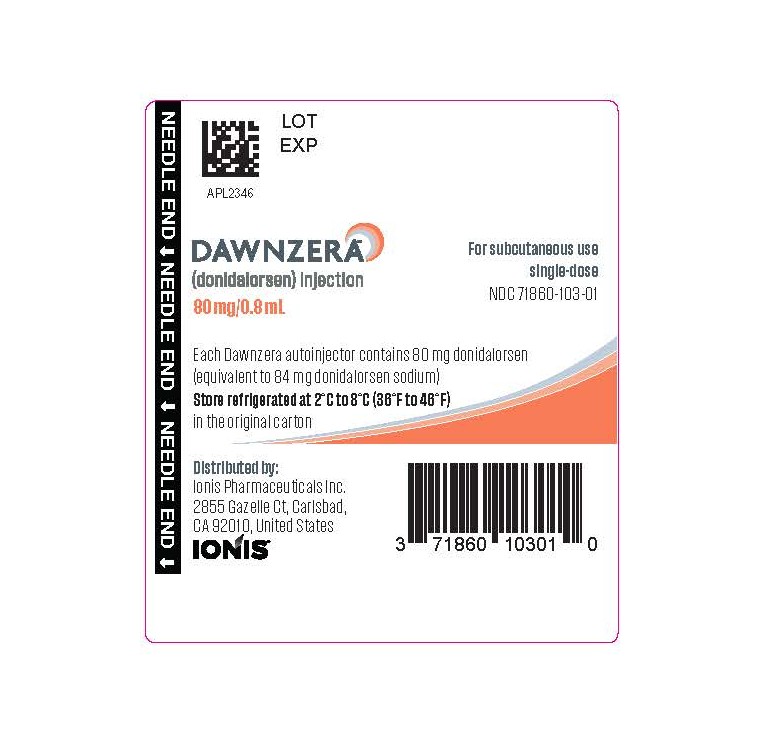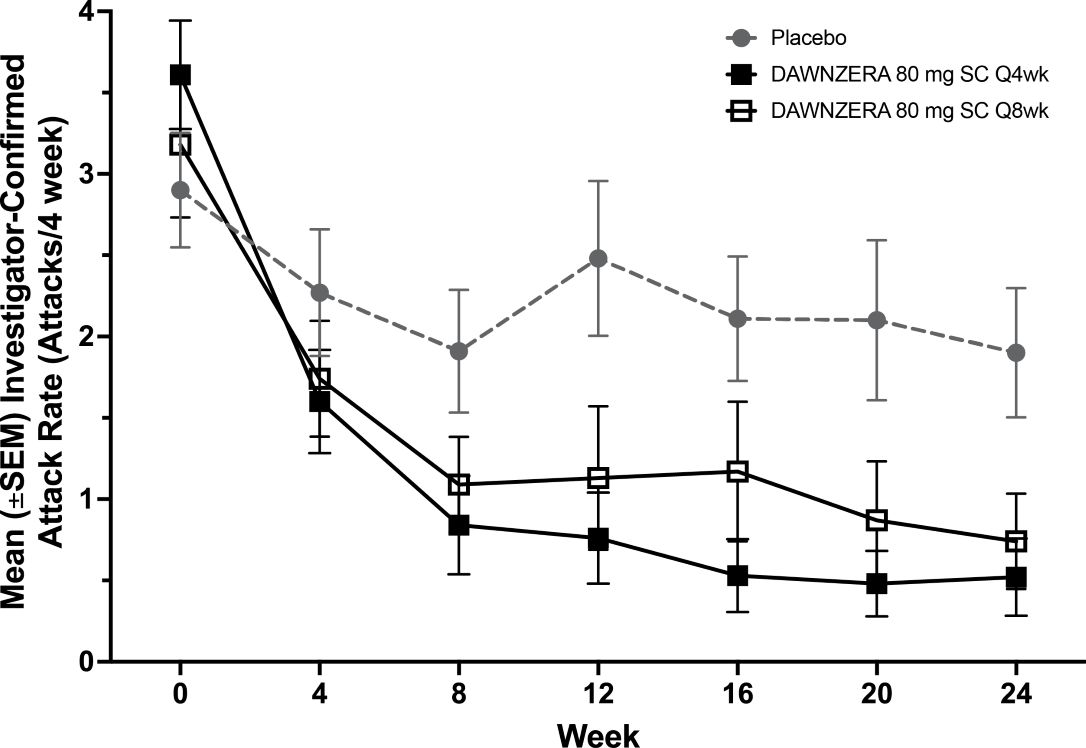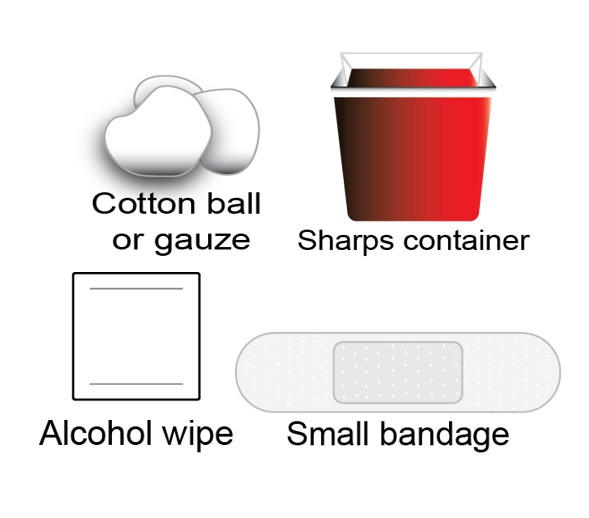 DRUG LABEL: DAWNZERA
NDC: 71860-103 | Form: INJECTION, SOLUTION
Manufacturer: Ionis Pharmaceuticals Inc.
Category: prescription | Type: HUMAN PRESCRIPTION DRUG LABEL
Date: 20250924

ACTIVE INGREDIENTS: DONIDALORSEN SODIUM 80 mg/0.8 mL
INACTIVE INGREDIENTS: SODIUM PHOSPHATE, MONOBASIC, UNSPECIFIED FORM; SODIUM PHOSPHATE, DIBASIC, ANHYDROUS; SODIUM CHLORIDE; HYDROCHLORIC ACID; SODIUM HYDROXIDE; WATER

HIGHLIGHTS OF PRESCRIBING INFORMATION

These highlights do not include all the information needed to use DAWNZERA™ (donidalorsen) safely and effectively. See full prescribing information for DAWNZERA.
DAWNZERA™ (donidalorsen) injection, for subcutaneous use
Initial U.S. Approval: 2025

1 INDICATIONS AND USAGE

DAWNZERA is a prekallikrein directed antisense oligonucleotide indicated for prophylaxis to prevent attacks of hereditary angioedema (HAE) in adult and pediatric patients 12 years of age and older. (1)

2 DOSAGE AND ADMINISTRATION

The recommended dosage of DAWNZERA is 80 mg administered subcutaneously every 4 weeks.

- A dosage of 80 mg every 8 weeks may also be considered. (2.1)
- See full prescribing information for administration instructions. (2.2)

3 DOSAGE FORMS AND STRENGTHS

Injection: 80 mg/0.8 mL solution in a single-dose autoinjector. (3)

4 CONTRAINDICATIONS

History of serious hypersensitivity reactions, including anaphylaxis, to donidalorsen or any of the excipients in DAWNZERA.

5 WARNINGS AND PRECAUTIONS

Hypersensitivity reactions including anaphylaxis have been reported following use of DAWNZERA. Advise patients to discontinue DAWNZERA and seek immediate medical attention if serious hypersensitivity reactions occur. (5.1)

6 ADVERSE REACTIONS

Most common adverse reactions (incidence ≥ 5%) are injection site reactions, upper respiratory tract infection, urinary tract infection, and abdominal discomfort. (6.1)

To report SUSPECTED ADVERSE REACTIONS, contact Ionis Pharmaceuticals at 1-833-644-6647 or FDA at 1-800-FDA-1088 or www.fda.gov/medwatch.

8 USE IN SPECIFIC POPULATIONS

Hepatic Impairment: Use in patients with moderate and severe hepatic impairment is not recommended. (8.7)

FULL PRESCRIBING INFORMATION

1 INDICATIONS AND USAGE

DAWNZERA™ is indicated for prophylaxis to prevent attacks of hereditary angioedema (HAE) in adult and pediatric patients 12 years of age and older.

2 DOSAGE AND ADMINISTRATION

2.1 Recommended Dosage

The recommended dosage of DAWNZERA is 80 mg administered subcutaneously every 4 weeks.

- A dosage of 80 mg administered subcutaneously every 8 weeks may be considered.

Missed Dose(s)

If a dose of DAWNZERA is missed, administer DAWNZERA as soon as possible. Resume treatment at the recommended dosing frequency from the date of the most recently administered dose.

2.2 Administration Instructions

- For subcutaneous use.
- DAWNZERA is intended for self-administration or administration by a caregiver. Prior to treatment initiation, train patients and/or caregivers on proper preparation and subcutaneous administration technique of DAWNZERA autoinjector [see Instructions for Use] .
- Remove the single‑dose autoinjector from the refrigerator 30 minutes prior to the injection and allow to warm to room temperature. Do not use other warming methods.
- Inspect DAWNZERA visually for particulate matter and discoloration prior to administration. The solution should appear clear and colorless to yellow. Do not use if cloudiness, particulate matter, or discoloration is observed prior to administration.
- Administer DAWNZERA subcutaneously into the abdomen or upper thigh region. The back of the upper arm can also be used as an injection site if a caregiver or healthcare provider administers the injection.

3 DOSAGE FORMS AND STRENGTHS

Injection: 80 mg/0.8 mL of donidalorsen as a sterile, clear, colorless to yellow solution in a single-dose autoinjector.

4 CONTRAINDICATIONS

DAWNZERA is contraindicated in patients with a history of serious hypersensitivity reactions, including anaphylaxis, to donidalorsen or any of the excipients in DAWNZERA [see Warnings and Precautions (5.1)and Adverse Reactions (6)] .

5 WARNINGS AND PRECAUTIONS

5.1 Risk of Hypersensitivity Reactions, Including Anaphylaxis

Hypersensitivity reactions, including anaphylaxis, have been reported in patients treated with DAWNZERA [see Adverse Reactions (6.1)] . If signs and symptoms of serious hypersensitivity reactions occur, discontinue DAWNZERA and institute appropriate therapy.

6 ADVERSE REACTIONS

The following clinically significant adverse reactions are discussed elsewhere in the labeling:

- Risk of Hypersensitivity Reactions, Including Anaphylaxis [see Warnings and Precautions (5.1)]

6.1 Clinical Trials Experience

Because clinical trials are conducted under widely varying conditions, adverse reaction rates observed in the clinical trials of a drug cannot be directly compared to rates in the clinical trials of another drug and may not reflect the rates observed in practice.

The safety of DAWNZERA reflects the exposure in a total of 171 adult and pediatric patients 12 years and older with hereditary angioedema (HAE) from a placebo-controlled trial (OASIS-HAE) [see Clinical Studies (14)] , and 2 other clinical studies. The average duration of DAWNZERA treatment exposure across the 3 clinical studies was 14 months.

The safety data below is based on the 24-week multicenter, randomized, double-blind, placebo-controlled trial (OASIS-HAE), in which patients received at least one subcutaneous dose of DAWNZERA 80 mg once every 4 weeks (n=45), DAWNZERA 80 mg once every 8 weeks (n=23), or matching placebo (n=22). Demographics of the patients in OASIS-HAE are summarized in Clinical Studies [see Clinical Studies (14)] .

Table 1 provides the most common adverse reactions with DAWNZERA with incidence ≥5% and more common than placebo.

Table 1: Adverse Reactions with DAWNZERA with Incidence ≥5% and More Common than Placebo in Patients with HAE (OASIS-HAE)
Adverse Reaction | DAWNZERA |  | Placebo (N=22)
Adverse Reaction | 80 mg q4wks (N=45) | 80 mg q8wks (N=23) | Placebo (N=22)
Adverse Reaction | n (%) | n (%) | n (%)
Injection site reactions*† | 11 (24) | 1 (4) | 1 (5)
Upper respiratory tract infection | 4 (9) | 2 (9) | 1 (5)
Urinary tract infection | 4 (9) | 2 (9) | 0
Abdominal discomfort | 3 (7) | 0 | 0
N = number of patients; n = number of patients experiencing the event; q4wks = every 4 weeks; q8wks = every 8 weeks.
* Injection site reactions include: erythema, discoloration, pain, pruritus, induration, bruising, haematoma, hypersensitivity, swelling, reaction, and urticaria.
† All injection site reactions were mild, nonserious, and the majority of them resolved without receiving any treatment.

Specific Adverse Reactions

Hypersensitivity Reactions, Including Anaphylaxis

In clinical trials, hypersensitivity reactions, including anaphylaxis, have occurred. Symptoms included generalized rash, dyspnea, chest pain, and peri-oral swelling.

Laboratory Tests

Decrease in Platelet Count: DAWNZERA can cause reductions in platelet count. In OASIS-HAE, the mean platelet count at baseline was 266,000/mm^3for the DAWNZERA 80 mg every 4 weeks group, 265,000/mm^3for the DAWNZERA 80 mg every 8 weeks group, and 245,000/mm^3for the placebo group. The mean percent change in platelet count at Week 25 was -9.6% for the DAWNZERA 80 mg every 4 weeks group, -7.9% for the DAWNZERA 80 mg every 8 weeks group, and -1.4% for the placebo group. In OASIS-HAE and 2 other clinical studies no DAWNZERA-treated patient had a platelet count of <50,000/mm^3, and there were no major bleeding events associated with a low platelet count.

Increase in Liver Function Tests: Increases from baseline in liver enzymes (alanine aminotransferase, aspartate aminotransferase, and gamma-glutamyl transferase) were observed with DAWNZERA use. The increased levels were generally below 3 times the upper limit of normal and stabilized. Discontinuations due to liver function test increases were infrequent.

8 USE IN SPECIFIC POPULATIONS

8.1 Pregnancy

Risk Summary

There are no available data on DAWNZERA use in pregnant women to evaluate for a drug-associated risk of major birth defects, miscarriage, or other adverse maternal or fetal outcomes.

In animal reproduction studies, subcutaneous administration of donidalorsen or a pharmacologically active mouse‑specific surrogate in a combined fertility and embryo‑fetal development study in mice and a pre‑ and postnatal development study in mice with F0 parental doses up to 5 times the maximum recommended human dose (MRHD, 80 mg) on a body surface area (BSA, mg/m^2) basis did not result in any adverse effects on embryofetal development, or behavioral, fertility, and reproductive development in the F1 offspring. Donidalorsen does not cross the placental barrier (see Data).

The estimated background risk of major birth defects and miscarriage for the indicated population(s) is unknown. All pregnancies have a background risk of birth defect, loss, or other adverse outcomes. In the U.S. general population, the estimated background risk of major birth defects and miscarriage in clinically recognized pregnancies is 2% to 4% and 15% to 20%, respectively.

Data

Animal Data

In reproductive toxicity studies with donidalorsen, the unconjugated form was not detected (below the limit of quantitation) in fetal tissues. Donidalorsen does not cross the placental barrier.

In a combined fertility and embryofetal development study, subcutaneous administration of donidalorsen (up to 10 mg/kg/week [2.5-times the MRHD on a BSA basis]) or a mouse‑specific surrogate (4 mg/kg/week) to male and female F0 mice weekly, prior to and during mating, and continuing every other day in females throughout the periods of implantation and organogenesis (Gestation Days 0 to 16), resulted in no adverse effects on embryofetal development. There was no evidence of maternal toxicity with doses up to 10 mg/kg/week.

In a pre- and postnatal development study, subcutaneous administration of donidalorsen (up to 20 mg/kg/week [5-times the MRHD on a BSA basis]) or a mouse-specific surrogate (5 mg/kg/week) to F0 female mice every other day throughout pregnancy (from Gestation Day 6 to 18) and weekly throughout lactation (from Lactation Day 1 to 20) produced no adverse effects on behavioral, fertility, and reproductive development in the F1 offspring. There was no evidence of maternal toxicity with doses up to 20 mg/kg/week.

8.2 Lactation

Risk Summary

There are no data on the presence of donidalorsen in human milk, the effects on the breast‑fed infant, or the effects on milk production. Donidalorsen was excreted into the milk of lactating mice; however, due to species-specific differences in lactation physiology, animal lactation data may not reliably predict levels in human milk (see Data). The developmental and health benefits of breastfeeding should be considered along with the mother’s clinical need for DAWNZERA and any potential adverse effects on the breast‑fed infant from DAWNZERA or from the underlying maternal condition.

Data

Animal Data

In the mouse pre‑ and postnatal development study, the concentrations of donidalorsen in breast milk from lactating mice on Lactation Day 15 increased in a dose‑dependent manner at doses ≥10 mg/kg/week, but these concentrations of donidalorsen in breast milk were lower than the observed concentrations in the liver where the drug is preferentially taken up. Even though donidalorsen was detected in the maternal mouse milk, systemic exposure in pups was not expected due to the lack of oral absorption of donidalorsen.

8.4 Pediatric Use

The safety and effectiveness of DAWNZERA for prophylaxis to prevent attacks of HAE have been established in pediatric patients aged 12 years and older. Use of DAWNZERA for this indication is supported by evidence from an adequate and well‑controlled trial (OASIS-HAE) that included 7 pediatric patients (aged 12 to 17 years) who received DAWNZERA 80 mg subcutaneously every 4 weeks (n=4) or every 8 weeks (n=3). The safety and effectiveness of DAWNZERA in pediatric patients aged 12 years and older is extrapolated from adults from OASIS-HAE with support from pharmacokinetic analysis and pharmacodynamic response [see Clinical Pharmacology (12.2, 12.3)and Clinical Studies (14)] . No new safety signals were identified in pediatric patients aged 12 years and older who received DAWNZERA [see Adverse Reactions (6.1)] .

The safety and effectiveness of DAWNZERA have not been established in pediatric patients younger than 12 years of age.

8.5 Geriatric Use

Clinical studies of DAWNZERA did not include sufficient numbers of patients 65 years of age and older to determine whether they respond differently from younger adult patients.

8.6 Renal Impairment

No dosage adjustment of DAWNZERA is recommended for patients with mild renal impairment (estimated glomerular filtration rate [eGFR] ≥60 to <90 mL/min/1.73 m^2) [see Clinical Pharmacology (12.3)] .

DAWNZERA has not been studied in patients with moderate or severe renal impairment or end‑stage renal disease.

8.7 Hepatic Impairment

No dosage adjustment of DAWNZERA is required for patients with mild hepatic impairment (defined by National Cancer Institute Organ Dysfunction Working Group [NCI-ODWG] Criteria: total bilirubin ≤1 × upper limit of normal [ULN] and aspartate aminotransferase [AST] >1 × ULN, or total bilirubin >1 to 1.5 × ULN and any AST level) [see Clinical Pharmacology (12.3)] .

DAWNZERA has not been studied in patients with moderate or severe hepatic impairment. Use of DAWNZERA is not recommended in patients with moderate or severe hepatic impairment (defined by NCI-ODWG Criteria: total bilirubin >1.5 x ULN regardless of AST level).

11 DESCRIPTION

Donidalorsen is a prekallikrein-directed antisense oligonucleotide (ASO) covalently linked to a ligand containing three N‑acetyl galactosamine (GalNAc) residues to facilitate delivery of the ASO to hepatocytes.

DAWNZERA contains donidalorsen sodium as the active ingredient. Donidalorsen sodium is a white to yellow solid and it is freely soluble in water and in sodium phosphate buffer. The molecular formula of donidalorsen sodium is C296H415N83O151P20S15Na20and the molecular weight is 9112.27 daltons. The chemical name of donidalorsen is DNA, d([2′- O-(2-methoxyethyl)]m^5rU-sp-[2′- O-(2-methoxyethyl)]rG-sp-[2′- O-(2-methoxyethyl)]m^5rC-[2′- O-(2-methoxyethyl)]rA-[2′- O-(2-methoxyethyl)]rA-sp-G-sp-T-sp-m^5C-sp-T-sp-m^5C-sp-T-sp-T-sp-G-sp-G-sp-m^5C-sp-[2′- O-(2-methoxyethyl)]rA-[2′- O-(2-methoxyethyl)]rA-[2′- O-(2methoxyethyl)]rA-sp-[2′- O-(2-methoxyethyl)]m^5rC-sp-[2′- O-(2-methoxyethyl)]rA), 5′-[26-[[2-(acetylamino)-2-deoxy-β-d-galactopyranosyl]oxy]-14,14-bis[[3-[[6-[[2-(acetylamino)-2-deoxy-β-d-galactopyranosyl]oxy]hexyl]amino]-3-oxopropoxy]methyl]-8,12,19-trioxo-16-oxa-7,13,20-triazahexacos-1-yl hydrogen phosphate], sodium salt (1:20).

The chemical structure of donidalorsen sodium is presented below:

DAWNZERA (donidalorsen) injection is a sterile, preservative‑free solution for subcutaneous injection supplied as a single-dose autoinjector. Each single‑dose autoinjector contains 80 mg of donidalorsen (equivalent to 84 mg donidalorsen sodium) in 0.8 mL of solution. The solution also contains disodium hydrogen phosphate; sodium chloride; sodium dihydrogen phosphate; water for injection; and may include hydrochloric acid and/or sodium hydroxide for pH adjustment between 6.9 to 7.9. Each dose of DAWNZERA injection contains 6 mg of phosphorous and 5 mg of sodium.

12 CLINICAL PHARMACOLOGY

12.1 Mechanism of Action

Donidalorsen is an ASO‑GalNAc conjugate that causes ribonuclease H1 (RNase H1)‑mediated degradation of PKK mRNA through binding to PKK mRNA, which results in reduced production of PKK protein. PKK is a pro‑enzyme for plasma kallikrein, which results in the release of bradykinin, a potent vasodilator causing swelling and pain in HAE. In patients with HAE, C1‑inhibitor (C1‑INH) deficiency or dysfunction leads to excessive plasma kallikrein activity, bradykinin generation, and angioedema attacks. Donidalorsen lowers PKK concentration, preventing excessive bradykinin production in patients with HAE.

12.2 Pharmacodynamics

In OASIS-HAE in adult and pediatric patients (≥12 years) with HAE‑1 or HAE‑2 [see Clinical Studies (14)] , a decrease in plasma PKK concentrations was observed at the first assessment (Week 4) following treatment with DAWNZERA 80 mg. The mean percentage reduction from baseline at Week 4 across both treatment groups was 48%. The mean percentage change from baseline to Week 24 in trough plasma PKK concentrations indicated reductions of 73% and 47% following treatment with DAWNZERA 80 mg every 4 weeks and every 8 weeks, respectively, compared with a slight increase (2%) observed in the placebo group.

Cardiac Electrophysiology

At the maximum recommended dose of DAWNZERA 80 mg every 4 weeks, clinically significant QTc interval prolongation was not observed.

12.3 Pharmacokinetics

The pharmacokinetic properties of DAWNZERA were evaluated following subcutaneous administration of multiple doses every 4 weeks in healthy subjects and every 4 weeks or every 8 weeks in patients with HAE. The pharmacokinetics of DAWNZERA were similar between healthy subjects and patients with HAE.

Donidalorsen exposure (area under the plasma concentration‑time curve [AUC]) at steady state following subcutaneous administration in healthy subjects increased in a greater than dose‑proportional manner over the dose range of 0.25 times the maximum recommended dosage to 80 mg every 4 weeks.

Geometric Mean (Coefficient of Variation [CV%]) of steady‑state maximum plasma concentration (Cmax,ss), trough plasma concentration (Ctrough,ss), and area under the plasma concentration‑time curve over the dosing interval (AUCτ,ss) are presented in Table 2. No accumulation of donidalorsen Cmaxand AUC was observed in plasma after repeated dosing every 4 weeks. However, a 2-fold increase of plasma donidalorsen Ctroughwas observed following repeated dosing every 4 weeks.

Table 2: Summary of Geometric Mean (CV%) Steady-State Donidalorsen Pharmacokinetic Parameters Following Dosage of DAWNZERA 80 mg Every 4 Weeks or 80 mg Every 8 Weeks in Patients with HAE
Pharmacokinetic Parameters (Geometric Mean) | DAWNZERA
Pharmacokinetic Parameters (Geometric Mean) | 80 mg q4wks | 80 mg q8wks
Cmax,ss(ng/mL) | 417 (81%) | 416 (78%)
Ctrough,ss(ng/mL) | 0.755 (63%) | 0.255 (73%)
AUCτ,ss(ng·h/mL) | 5240 (52%) | 5210 (52%)
AUCτ,ss= area under the plasma concentration time curve over each dosing interval at steady state; Cmax,ss= maximum plasma concentration at steady state; Ctrough,ss= trough plasma concentration at steady state; q4wks = every 4 weeks; q8wks = every 8 weeks.

Absorption

Following subcutaneous administration, donidalorsen is absorbed with the median (range) time to maximum plasma concentration of approximately 2 (0.25, 8) hours post dose.

Distribution

Donidalorsen is expected to distribute primarily to the liver and kidney cortex after subcutaneous dosing. The apparent volume of distribution for the central (Vc/F) and peripheral (Vp/F) compartment were 69.8 L and 1840 L, respectively. Donidalorsen is highly bound to human plasma proteins (>98% bound) in vitro.

Elimination

The terminal plasma elimination half-life of donidalorsen in a typical patient with HAE is approximately 1 month. The half-life of the initial rapid clearance phase, reflecting tissue distribution, was approximately 5 hours.

Metabolism

The oligonucleotide moiety of donidalorsen is expected to be metabolized by endo‑ and exonucleases to short oligonucleotide fragments of varying sizes within the liver. Based on in vitrostudies, donidalorsen is not a substrate of cytochrome P450 (CYP) enzymes.

The linker that covalently connects the ASO to the GalNAc residues is cleaved via hydrolysis and undergoes dephosphorylation and subsequent oxidative metabolism to form inactive metabolites, which are minimally released in circulation. The most abundant linker-related metabolite (M8) is a substrate of CYP3A4.

Excretion

The mean fraction of unchanged ASO eliminated in urine was less than 1% of the administered dose in healthy subjects within 24 hours post-dose. The renal route of elimination is minor for linker-related metabolites.

Specific Populations

No clinically meaningful differences in the pharmacokinetics or pharmacodynamics of donidalorsen were observed based on age (12 to 68 years), body weight (37 to 152 kg), sex, race (68% White, 24% Black, and 4% Asian), ethnicity, disease status (healthy subjects or subjects with HAE), mild renal impairment (eGFR ≥60 to <90 mL/min/1.73 m^2), or mild hepatic impairment (defined using NCI-ODWG Criteria: total bilirubin ≤1 × ULN and AST >1 × ULN, or total bilirubin >1 to 1.5 × ULN and any AST).

Donidalorsen has not been studied in patients with moderate or severe renal impairment, end‑stage renal disease, or moderate or severe hepatic impairment.

Drug Interaction Studies

No clinical drug‑drug interaction studies have been performed with donidalorsen. In vitrostudies show that donidalorsen is not a substrate or inhibitor of transporters, does not interact with highly plasma protein bound drugs, and is not an inhibitor/inducer of CYP enzymes. In vitro studies show that linker-related metabolite M8 is not an inhibitor or inducer of CYP enzymes. M8 is a substrate of transporters bile salt export pump (BSEP) and organic anion transporting polypeptide 1B3 (OATP1B3), and is an inhibitor of multidrug and toxin extrusion protein 1 (MATE1) transporter.

12.6 Immunogenicity

The observed incidence of anti‑drug antibodies (ADAs) is highly dependent on the sensitivity and specificity of the assay. Differences in assay methods preclude meaningful comparisons of the incidence of anti-drug antibodies in the studies described below with the incidence of anti-drug antibodies in other studies, including those of donidalorsen or of other donidalorsen products.

In OASIS-HAE, with a treatment duration up to 24 weeks, the incidence rate of treatment‑emergent ADAs in adult and pediatric patients (≥12 years of age) with HAE was 20% (9 of 45 patients) in the DAWNZERA 80 mg every 4 weeks group and 22% (5 of 23 patients) in the DAWNZERA 80 mg every 8 weeks group. In an open‑label extension trial, patients that rolled over from OASIS-HAE continued treatment with DAWNZERA in the 80 mg every 4 weeks or every 8 weeks groups for up to 3 years (median exposure duration of 227 days). The incidence rate of treatment‑emergent ADAs was 35% (22 of 63 patients) in the DAWNZERA 80 mg every 4 weeks group, including patients initially randomized to DAWNZERA 80 mg every 4 weeks in OASIS-HAE (36%, 16/44) and patients initially randomized to placebo in OASIS-HAE (32%, 6/19). The incidence rate of treatment-emergent ADAs was 21% (3 of 14 patients) among patients who received DAWNZERA 80 mg every 8 weeks in OASIS-HAE and open-label extension.

In general, the development of ADAs was not found to affect the pharmacodynamics, safety, or efficacy of DAWNZERA. An increase in donidalorsen plasma Ctroughwas observed in ADA-positive patients with high titers. Because of small sample size, the effect of ADA on the pharmacokinetics, pharmacodynamics, safety and effectiveness of DAWNZERA is inconclusive.

13 NONCLINICAL TOXICOLOGY

13.1 Carcinogenesis, Mutagenesis, Impairment of Fertility

Carcinogenesis

In a 6-month carcinogenicity study in transgenic (Tg.rasH2) mice, subcutaneous administration of donidalorsen, up to the highest dose tested (20 mg/kg in males and 60 mg/kg in females) or a mouse-specific surrogate (10 mg/kg) once every 2 weeks did not result in an increase in malignant tumors.

Mutagenesis

Donidalorsen was negative for genotoxicity in the in vitrobacterial reverse mutation test and chromosomal aberration assay in Chinese hamster lung cells and in vivomouse bone marrow micronucleus assay.

Fertility

Fertility and reproductive performance were unaffected by subcutaneous administration of donidalorsen (up to 10 mg/kg/week [2.5-times the MRHD on a BSA basis]) or a mouse‑specific surrogate (4 mg/kg/week) to male and female mice weekly, prior to and during mating, and continuing every other day in females throughout the periods of implantation and organogenesis.

14 CLINICAL STUDIES

The efficacy of DAWNZERA for prophylaxis to prevent attacks of hereditary angioedema (HAE) in adult and pediatric patients 12 years of age and older was evaluated in a 24‑week multicenter, randomized, double‑blind, placebo‑controlled trial (OASIS-HAE [ NCT05139810]).

The trial (OASIS-HAE) included 90 adult and pediatric patients 12 years of age and older with Type I and Type II HAE, who had at least 2 investigator‑confirmed attacks during the 8‑week run‑in period. Patients were randomized to receive DAWNZERA 80 mg once every 4 weeks (n=45), DAWNZERA 80 mg once every 8 weeks (n=23), or matching placebo (n=22). Patients were required to discontinue other prophylactic HAE medications, except androgens and tranexamic acid, prior to entering the trial; all patients were allowed to use rescue medications for treatment of breakthrough HAE attacks.

The demographics and baseline characteristics of OASIS-HAE trial are provided in Table 3.

Table 3: Demographics and Baseline Characteristics of Patients in the OASIS-HAE Trial
 | OASIS-HAE (N=90)
Female, n (%) | 48 (53)
Race, n (%)
Asian | 1 (1)
Black or African American | 2 (2)
White | 82 (91)
American Indian or Alaskan Native Asian | 3 (3)
Multiple | 1(1)
Other | 1(1)
Hispanic or Latino, n (%) | 6 (7)
Mean age, years (SD) | 37 (14)
≤ 17 years, n (%) | 7 (8)
> 17 years, n (%) | 83 (92)
C1-INH HAE Type 1, n (%) | 84 (93)
Prior HAE prophylaxis*, n (%) | 16 (18)
Baseline HAE attack rate**, n (%)
≤ 2 attacks/4 weeks | 28 (31)
2 to 5 attacks/4 weeks | 48 (53)
≥ 5 attacks/4 weeks | 14 (16)
* Within 5 half-lives of screening (up to 10 weeks).
**Period from screening to first dose.

The primary endpoint for OASIS-HAE was the HAE attack rate (number of investigator-confirmed HAE attacks per 4 weeks) from Week 0 to Week 24. As shown in Table 4, DAWNZERA 80 mg administered subcutaneously every 4 or 8 weeks demonstrated statistically significant reductions in the HAE attack rate compared to placebo.

Table 4: HAE Attack Rate (Attacks/4 Weeks) at Week 24 in OASIS-HAE
 | DAWNZERA 80 mg q4wks (N=45) | DAWNZERA 80 mg q8wks (N=23) | Placebo (N=22)
HAE Attack Rate per 4 Weeks from Week 0 to Week 24*
LS mean (95% CI) attack rate | 0.44 (0.27, 0.73) | 1.02 (0.65, 1.59) | 2.26 (1.66, 3.09)
% Reduction (95% CI) relative to placebo† | -81 (-89, -65) | -55 (-74, -22) | --
Wald chi-square p-value | <0.001 | 0.004 | --
CI = confidence interval; HAE = hereditary angioedema; LS = least square; N = number of patients in the specific treatment group; q4wks = every 4 weeks; q8wks = every 8 weeks.
* Primary efficacy endpoint = comparison of the time-normalized number of investigator-confirmed HAE attacks per 4 weeks from Week 0 to Week 24 between the DAWNZERA 80 mg q4wks group and the placebo group.
† Calculated as the ratio of the model-based treatment period HAE attack rates (donidalorsen/placebo) minus 1 multiplied by 100.

The mean decreases from baseline in the HAE attack rate observed throughout the treatment period in the DAWNZERA treatment groups are shown in Figure 1.

Figure 1: Mean (± SEM) Investigator‑confirmed HAE Attack Rate (Attacks/4 Weeks) in OASIS-HAE

HAE = hereditary angioedema; q4wks = every 4 weeks; q8wks = every 8 weeks; SC = subcutaneous; SEM = standard error of the mean.

Pre-defined secondary endpoints were assessed from Week 4 to Week 24. The moderate or severe HAE attack rate was 0.12 for the DAWNZERA 80 mg every 4 weeks group, 0.68 for the DAWNZERA 80 mg every 8 weeks group, and 1.15 for the placebo group, representing a reduction of 89% (95% CI: 66, 97) and 41% (95% CI: -26, 72) in moderate or severe HAE attack rate relative to placebo, respectively. The HAE attacks requiring acute therapy was 0.15 for the DAWNZERA 80 mg every 4 weeks group, 0.59 for the DAWNZERA 80 mg every 8 weeks group, and 1.80 for the placebo group, representing a reduction of 92% (95% CI: 77, 97) and 67% (95% CI: 29, 85) in HAE attacks requiring acute therapy relative to placebo, respectively.

The proportion of patients who were attack-free from Week 4 to Week 24 were 53% in the DAWNZERA 80 mg every 4 weeks group, 35% in the DAWNZERA 80 mg every 8 weeks group, and 9% in the placebo group, representing an odds ratio of being attack-free of 11.79 (95% CI: 2.34, 59.36) and 3.23 (95% CI: 0.46, 22.85), respectively.

The proportion of patients with a ≥50%, ≥70%, and ≥90% reduction from baseline to Week 4 through Week 24 was 93%, 82%, and 62% in the DAWNZERA 80 mg every 4 weeks group, 83%, 65%, and 48% in the DAWNZERA 80 mg every 8 weeks group, and 27%, 18%, and 9% in the placebo group, respectively.

16 HOW SUPPLIED/STORAGE AND HANDLING

How Supplied

DAWNZERA (donidalorsen) 80 mg/0.8 mL injection is a sterile, preservative‑free, clear, colorless to yellow solution supplied in a single‑dose autoinjector. Each autoinjector of DAWNZERA is filled to deliver 0.8 mL of solution containing 80 mg of donidalorsen. Table 5 provides the presentation and strength for DAWNZERA.

Table 5: Presentation and Strength for DAWNZERA
Presentation | Strength | Unit Count | NDC
Autoinjector | 80 mg/0.8 mL | 1 | 71860-103-01

Storage and Handling

- Store the DAWNZERA autoinjector in the refrigerator between 36°F to 46°F (2°C to 8°C) in the original carton.
- The DAWNZERA autoinjector can be stored at room temperature up to 86°F (30°C) in the original carton for up to 6 weeks; if not used within the 6 weeks stored at room temperature, discard DAWNZERA.
- Do not freeze. Do not expose to heat. Protect from direct light.

17 PATIENT COUNSELING INFORMATION

Advise the patient to read the FDA‑approved patient labeling (Patient Information and Instructions for Use).

Administration Instructions

- Instruct patients that DAWNZERA is for subcutaneous use and intended for self-administration or administration by a caregiver.
- Instruct patients and/or caregivers on proper preparation and subcutaneous administration technique of DAWNZERA autoinjector [see Dosage and Administration (2.2)and Instructions for Use] .
- Instruct patients to administer DAWNZERA subcutaneously into the abdomen or upper thigh region for self-administration. The back of the upper arm can be used as an injection site if a caregiver or healthcare provider administers DAWNZERA.

Missed Dose(s)

Instruct patients to use DAWNZERA as prescribed. If a dose is missed, instruct patients to administer DAWNZERA as soon as they remember. Instruct patients to resume treatment at the recommended dosing frequency (every 4 weeks or every 8 weeks) from the date of the most recently administered dose [see Dosage and Administration (2.1)] .

Risk of Hypersensitivity Reactions, Including Anaphylaxis

Advise patients hypersensitivity reactions, including anaphylaxis, have been reported following administration of DAWNZERA. Instruct patients to immediately discontinue DAWNZERA and seek medical attention if they experience signs and symptoms of serious hypersensitivity reaction [see Warnings and Precautions (5.1)] .

Distributed by: Ionis Pharmaceuticals Inc., Carlsbad, CA 92010

DAWNZERA is a trademark of Ionis Pharmaceuticals Inc. All other trademarks are the property of their respective owners.

©2025 Ionis Pharmaceuticals Inc.

Instructions for Use

DAWNZERATM[dawn-ZAIR-ah]

(donidalorsen)

injection, for subcutaneous use

This Instructions for Use contains information on how to inject DAWNZERAusing the autoinjector.

Read this Instructions for Use before you start using your DAWNZERA autoinjector and each time you get a refill. There may be new information.This information does not take the place of talking to your healthcare provider about your medical condition or treatment. Your healthcare provider should show you or your caregiver how to use the DAWNZERA autoinjector the right way. If you or your caregiver have any questions, talk to your healthcare provider.

Important information:

- DAWNZERA is injected under the skin (subcutaneous use) only.
- Each autoinjector contains 1 single-dose and can only be used 1 time.
- Do notremove the clear cap until you are ready to inject DAWNZERA (See Step 5).
- Do notshare your autoinjector with anyone.
- Do notuse if the autoinjector appears damaged.

Storage information:

- Store the autoinjector in the refrigerator between 36°F to 46°F (2°C to 8°C) in the original carton.
- If needed, DAWNZERA can be storedat room temperature up to 86°F (30°C) in the original carton for up to 6 weeks.
- Do notstore DAWNZERA at room temperatures above 86°F.
- Throw away the DAWNZERA if kept at room temperature longer than 6 weeks.
- Do notfreeze.
- Donotexpose the autoinjector to heat.
- Protect from direct light.
- Keep the autoinjector in the carton until ready to use.
- Do notstore the autoinjector with the clear cap removed.

Keep DAWNZERA and all medicine out of the reach of children.

Parts of your DAWNZERA autoinjector

Single-dose autoinjector

Other supplies (not included)

Preparing to inject DAWNZERA

Step 1 Remove fromthe refrigerator 30 minutes before you inject

a) Remove the autoinjector from the refrigerator.

b) Keep the autoinjector in the original cartonand let the autoinjector come to room temperature for 30 minutes before injecting.

Do nottry to speed up the warming process using other heat sources, such as a microwave or hot water.

Step 2 Check the medicine

a)Check the expiration (EXP) date.

b)Check the medicine through the viewing window. The DAWNZERA medicine should be clear and colorless to yellow. There should be no particles. It is normal to see air bubbles in the solution.

Do notuse the autoinjector if the:

- clear cap is missing or not attached.
- expiration (EXP) date has passed.
- medicine looks cloudy, discolored, or has particles.
- autoinjector appears damaged.

Step 3 Choose the injection site

a)Choose an injection site on the stomach or the front of the thigh.

b) Only healthcare providers or caregivers may choose the back of the upper arm.

Do notinject:

- within 2 inches of the belly button (navel).
- into skin that is bruised, tender, red, or hard.
- into scars or damaged skin.

Step 4 Wash hands and clean the injection site

a)Wash your hands with soap and water.

b)Clean the injection site with an alcohol wipe in a circular motion. Let the skin air dry.

Do nottouch the cleaned skin before injecting.

Injecting DAWNZERA

Step 5 Remove and throw away the clear cap

a)Hold the autoinjector by the middle with the clear cap facing away from you.

b)Remove the clear cap by pulling it straight off. Do nottwist it off. The needle is inside the orange needle shield.

c)Throw away the clear cap in the trash or sharps container.

Do not remove the clear cap until right before you inject.
Do notrecap the autoinjector.
Do notpush the orange needle shield against the hand or finger.

Step 6 Begin injection

a)Hold the autoinjector in 1 hand. Place the orange needle shield at a 90 degree angle against your skin. Make sure you can see the viewing window.

b)Push firmly and hold the autoinjector straight against the skin. You will hear a click as the injection starts.

You may hear a second click. This is normal. The procedure is not finished.

c)Hold the autoinjector against the skin for 10 seconds to make sure the full dose has been given.

Do notmove, turn, or change the angle of the autoinjector during the injection.

Step 7 Finish injection

a)Check that the orange plunger rod

has moved down to fill the entire viewing window.

- If the orange plunger rod does not fill the viewing window, you may not have received the full dose.
- If this happens or if you have other concerns, contact your healthcare provider.

b)Remove the autoinjector by lifting it straight up. After removal from the skin, the orange needle shield locks into place and covers the needle.

c)There may be a small amount of blood or liquid where you injected. This is normal.

If needed, press a cotton ball or gauze on the area and apply a small bandage.

The autoinjector contains 1 dose. Do notreuse the autoinjector.

Step 8 Throwing away autoinjector

a)Put the used autoinjector in a sharps container right away after use.

Do notthrow away the autoinjector in your household trash.
Do notrecycle your used sharps disposal container.
Do notreuse the autoinjector or clear cap.

If you do not have an FDA-cleared sharps container, you may use a household container that is:

- made of a heavy-duty plastic,
- can be closed with a tight-fitting, puncture-resistant lid, without sharps being able to come out,
- upright and stable during use,
- leak-resistant, and
- properly labelled to warn of hazardous waste inside the container.

When your sharps disposal container is almost full, you will need to follow your community guidelines for the right way to dispose of your sharps disposal container. There may be state or local laws about how you should throw away used autoinjectors.

For more information about safe sharps disposal, and specific information about sharps disposal in the state that you live in, go to the FDA's website at: http://www.fda.gov/safesharpsdisposal.

Do notthrow away your used sharps disposal container in your household trash unless your community guidelines permit this. Do notrecycle your used sharps disposal container.

For more information, go to https://www.DAWNZERA.com or call 1-833-644-6647. If you still have questions, contact your healthcare provider.

Distributed by: Ionis Pharmaceuticals, Inc., Carlsbad, CA 92010

This Instructions for Use has been approved by the U.S. Food and Drug Administration Approved: 08/2025

Patient Information

DAWNZERATM (dawn-ZAIR-ah)
(donidalorsen)
injection, for subcutaneous use

What is DAWNZERA?

DAWNZERA is a prescription medicine used to prevent hereditary angioedema (HAE) attacks in adults and children 12 years of age and older.

It is not known if DAWNZERA is safe and effective in children under 12 years of age.

Do not use DAWNZERA if you:

- have had a serious allergic reaction, including anaphylaxis to donidalorsen or any of the ingredients in DAWNZERA. See the end of this Patient Information leaflet for a complete list of ingredients in DAWNZERA.

Before using DAWNZERA, tell your healthcare provider about all your medical conditions, including if you:

- are pregnant or plan to become pregnant. It is not known if DAWNZERA can harm your unborn baby. Tell your healthcare provider if you become pregnant during treatment with DAWNZERA.
- are breastfeeding or plan to breastfeed. It is not known if DAWNZERA passes into your breast milk. Talk to your healthcare provider about the best way to feed your baby while using DAWNZERA.

Tell your healthcare provider about any other medications you take,including prescription and over‑the‑counter medicines, vitamins, and herbal supplements. Know the medicines you take. Keep a list of them to show your healthcare provider and pharmacist when you get a new medicine.

How should I use DAWNZERA?

- Read the detailed Instructions for Use that comes with your DAWNZERA single-dose autoinjector.
- Your healthcare provider will show you and your caregiver how to inject DAWNZERA the first time.
- DAWNZERA is injected under your skin (subcutaneous use) in your stomach area (abdomen) or the front of your upper legs (thighs). Only a healthcare provider or caregiver may give you an injection in the back of your upper arm.
- Use DAWNZERA exactly as your healthcare provider tells you to take it.
- You, your caregiver, or healthcare provider should inject DAWNZERA 1 time every 4 weeks or 1 time every 8 weeks depending on your prescribed dosing frequency.
- If you miss a dose of DAWNZERA, take the missed dose as soon as possible. Then inject DAWNZERA on the regular dosing schedule from the date of the most recently injected dose.

What are the possible side effects of DAWNZERA?

DAWNZERA can cause serious side effects, including:

- Allergic reactions.DAWNZERA can cause allergic reactions. Stop taking DAWNZERA and call your healthcare provider or go to your nearest emergency room right away if you have symptoms of serious allergic reaction. Symptoms of serious allergic reaction may include:

o rash
o trouble breathing
o fainting, dizziness, feeling lightheaded (low blood pressure)

o swelling of your face, lips, or tongue
o chest pain
o itching

The most common side effects of DAWNZERAinclude:

o injection site reactions
o upper respiratory tract infection

o urinary tract infection
o abdominal discomfort

These are not the only possible side effects of DAWNZERA. Tell your healthcare provider if you have any side effect that bothers you or that does not go away while using DAWNZERA.

Call your doctor for medical advice about side effects. You may report side effects to FDA at 1-800-FDA-1088.

How should I store DAWNZERA?

- Store DAWNZERA in the refrigerator between 36°F to 46°F (2°C to 8°C) in the original carton.
- If needed, DAWNZERA can be stored at room temperature up to 86°F (30°C) in the original carton for up to 6 weeks. If not used within 6 weeks, throw away DAWNZERA.
- Do not freeze.
- Do not expose the autoinjector to heat.
- Protect from direct light.

Keep DAWNZERA and all medicines out of the reach of children.

General information about the safe and effective use of DAWNZERA.
Medicines are sometimes prescribed for purposes other than those listed in a Patient Information leaflet. Do not use DAWNZERA for a condition for which it was not prescribed. Do not give DAWNZERA to other people, even if they have the same symptoms or condition that you have. It may harm them. You can ask your pharmacist or healthcare provider for information about DAWNZERA that is written for health professionals.

What are the ingredients in DAWNZERA?
Active ingredients: donidalorsen

Inactive ingredients: disodium hydrogen phosphate; sodium chloride; sodium dihydrogen phosphate; water for injection; and may include hydrochloric acid or sodium hydroxide. Phosphorous and sodium.

Distributed by: Ionis Pharmaceuticals Inc.

DAWNZERA is a trademark of Ionis Pharmaceuticals Inc.

For more information go to www.DAWNZERA.com or call 1-833-644-6647. If you still have questions, contact your healthcare provider.

This Patient Information has been approved by the U.S. Food and Drug Administration Issued: 08/2025

PRINCIPAL DISPLAY PANEL

DAWNZERA™

(donidalorsen) 80mg/0.8mL
injection for subcutaneous use

1 single-dose autoinjector

Each Dawnzera autoinjector contains 80 mg donidalorsen (equivalent to 84 mg donidalorsen
sodium) in 0.8 mL of solution, single-dose, and is for the treatment of adult and adolescent
patients with HAE.
Store refrigerated at 2ºC to 8ºC (36ºC to 46ºC) in the orignal container and protect from direct light.
Do not freeze.

IONIS

Rx Only DAWNZERA™(donidalorsen) 80 mg/0.8ml

injection for subcutaneous use

Each Dawnzera autoinjector contains 80 mg donidalorsen
(equivalent to 84 mg donialorsen sodium)
Store refrigerated at 2ºC to 8ºC (36ºC to 46ºC)
in the original container

Distributed by: NDC71860-103-01
Ionis Pharmaceuticals Inc.
2855 Gazelle Ct, Carlsbad, CA 92010,
United States IONIS